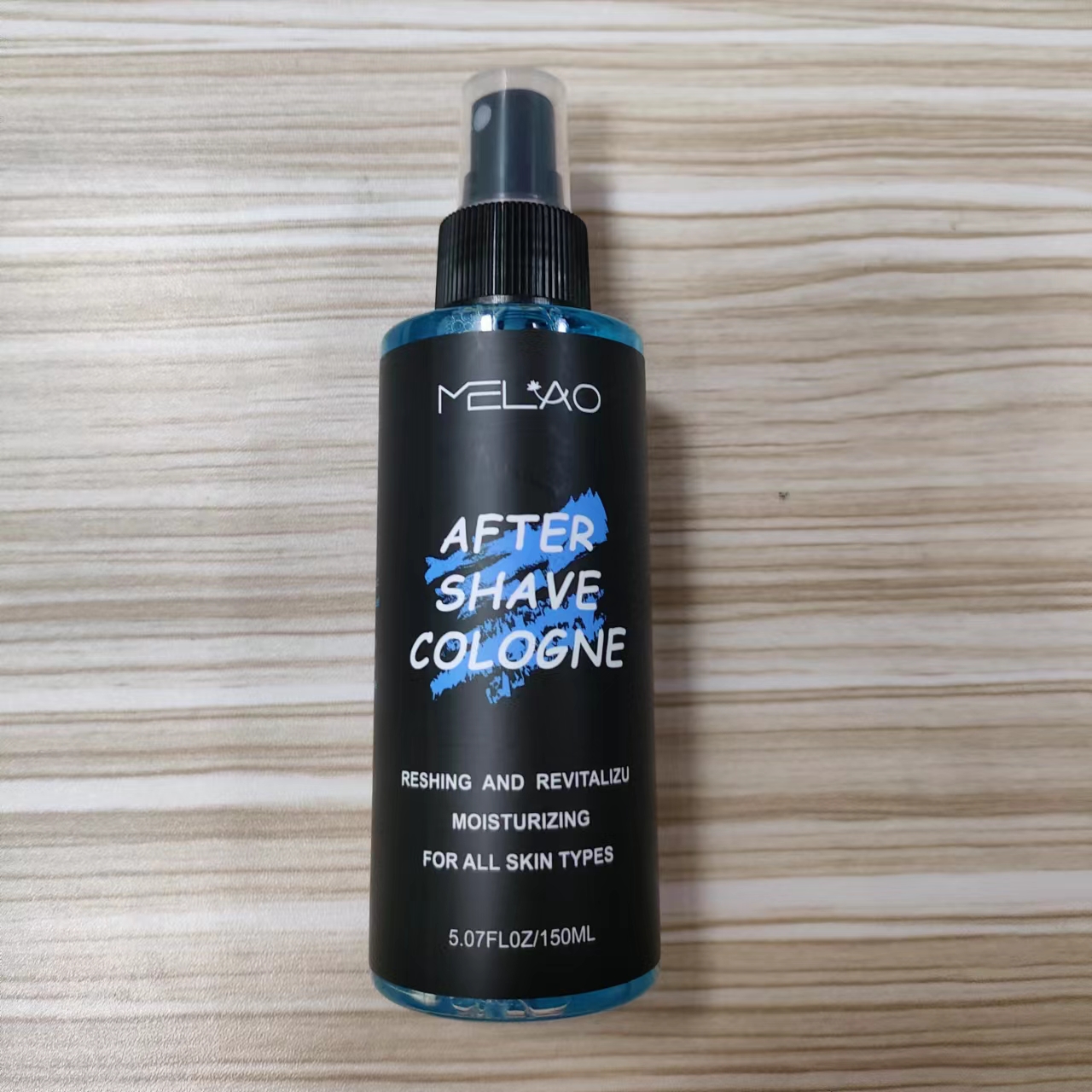 DRUG LABEL: MELAO AFTER  SHAVE COLOGNE
NDC: 74458-454 | Form: SPRAY
Manufacturer: Guangzhou Yilong Cosmetics Co., Ltd
Category: otc | Type: HUMAN OTC DRUG LABEL
Date: 20241005

ACTIVE INGREDIENTS: GLYCYRRHIZINATE DIPOTASSIUM 0.5 g/100 mL
INACTIVE INGREDIENTS: WATER; ALOE VERA LEAF; GLYCERIN; 1,2-HEXANEDIOL; STEPHANIA TETRANDRA ROOT; TARAXACUM OFFICINALE LEAF; 2-HYDROXYACETOPHENONE; HYDROGENATED CASTOR OIL; FRAGRANCE 13576; CHLORPHENESIN; ERYTHRITOL; SAURURUS CHINENSIS WHOLE; BUTYLENE GLYCOL

MELAO AFTER SHAVE COLOGNE

ACTIVE INGREDIENT

GLYCYRRHIZINATE DIPOTASSIUM 0.5%

INACTIVE INGREDIENT

Water

Aloe Barbadensis Leaf Juice

Glycerin

Erythritol

Butylene Glycol

Saururus Chinensis Leaf/Root Extract

Taraxacum Officinale (Dandelion) Leaf Extract

Hydroxyacetophenone

1,2-Hexanediol

Stephania Tetrandra Root Extract

PEG-40 Hydrogenated Castor Oil

Chlorphenesin

Fragrance

PURPOSE

Calms the skin after shaving.

INDICATIONS AND USAGE

After shaving, rinse with cold water.Pat dry your face and pour the After Shave Cologne onto your palm and rub your palms together.Finally, applyevenly and massage it into your skin.

WARNINGS

For external use only.

Stop use and ask a doctor if rash occurs.

Do not use on damaged or broken skin.

When using this product keep out of eyes. Rinse with water to remove.

Keep out of reach of children. If swallowed, get medical help or contact a Poison Control Center right away.

DOSAGE AND ADMINISTRATION

After shaving, rinse with cold water.Pat dry your face and pour the After Shave Cologne onto your palm and rub your palms together.Finally, applyevenly and massage it into your skin.